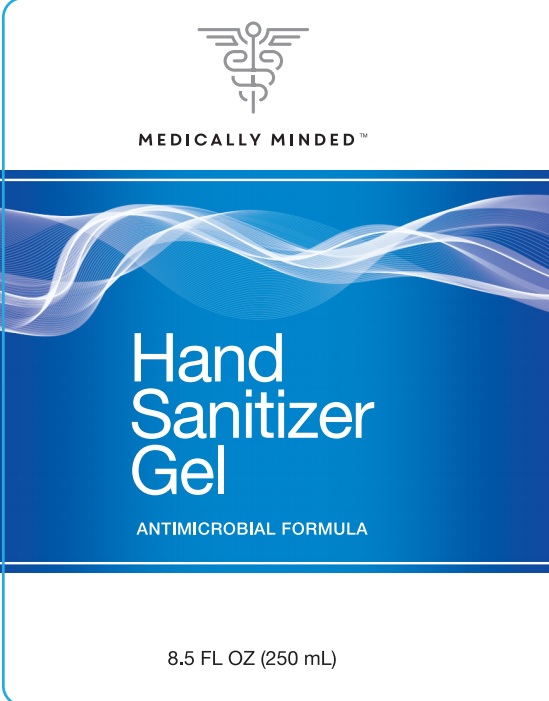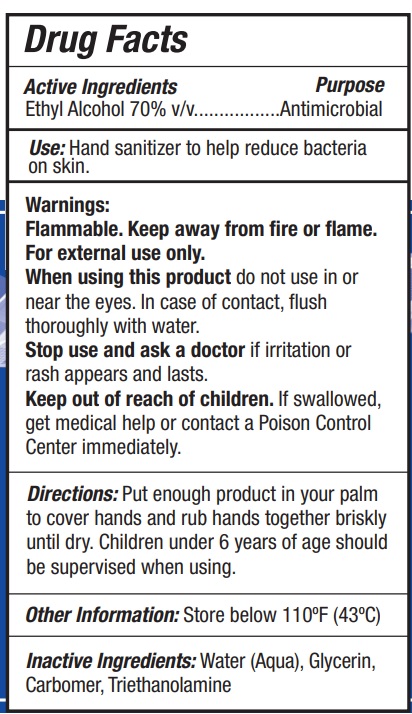 DRUG LABEL: MEDICALLY MINDED
NDC: 76619-110 | Form: GEL
Manufacturer: SBL LLC
Category: otc | Type: HUMAN OTC DRUG LABEL
Date: 20200714

ACTIVE INGREDIENTS: ALCOHOL 0.7 mL/1 mL
INACTIVE INGREDIENTS: WATER 0.4 mL/1 mL; TROLAMINE 0.0025 mL/1 mL; CARBOMER HOMOPOLYMER, UNSPECIFIED TYPE 0.002 mL/1 mL; PHENOXYETHANOL 0.0003 mL/1 mL; ALOE VERA LEAF 0.001 mL/1 mL

HAND SANITIZER

ANTIMICROBIAL FORMULA

8.5 FL OZ (250 ML)

Active Ingredient(s)

Alcohol 70% v/v. Purpose: Antimicrobial

Purpose

Hand Sanitizer Antimicrobial

Use

Hand Sanitizer to help reduce bacteria that potentially can cause disease. For use when soap and water are not available.

Warnings

Warnings: Flammable. Keep away from fire or flame. For external use only. When using this product do not use in or near the eyes. In case of contact, flush thoroughly with water. Stop use and ask a doctor if irritation or rash appears and lasts. Keep out of reach of children. If swallowed, get medical help or contact a Poison Control Center immediately.

Do not use

- in children less than 2 months of age
- on open skin wounds

When using this product keep out of eyes, ears, and mouth. In case of contact with eyes, rinse eyes thoroughly with water.
Stop use and ask a doctor if irritation or rash occurs. These may be signs of a serious condition.
Keep out of reach of children. If swallowed, get medical help or contact a Poison Control Center right away.

Stop use and ask a doctor if irritation or rash occurs. These may be signs of a serious condition.

Keep out of reach of children. If swallowed, get medical help or contact a Poison Control Center right away.

Directions

- Place enough product on hands to cover all surfaces. Rub hands together until dry.
- Supervise children under 6 years of age when using this product to avoid swallowing.

Other information

- Store between 15-30C (59-86F)
- Avoid freezing and excessive heat above 40C (104F)

Inactive ingredients

Inactive Ingredients: Water (Aqua), Glycerin, Carbomer, Triethanolamine

Package Label - Principal Display Panel

HAND SANITIZER

ANTIMICROBIAL FORMULA

8.5 FL OZ (250 ML)